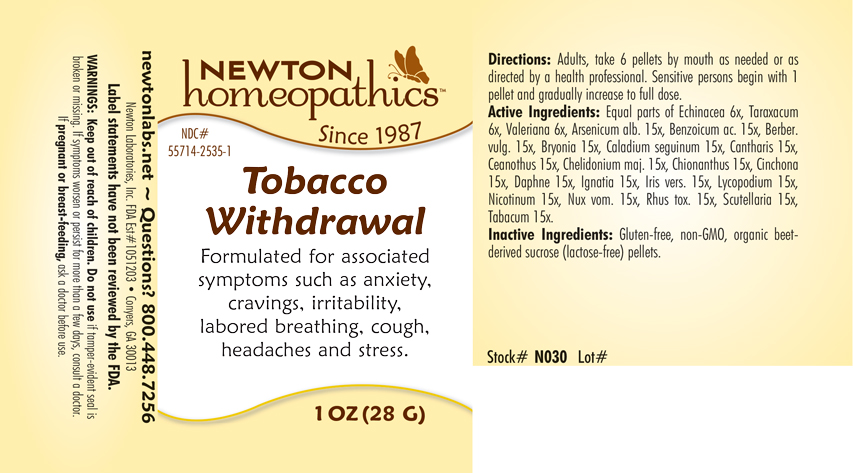 DRUG LABEL: Tobacco Withdrawal
NDC: 55714-2535 | Form: PELLET
Manufacturer: Newton Laboratories, Inc.
Category: homeopathic | Type: HUMAN OTC DRUG LABEL
Date: 20250210

ACTIVE INGREDIENTS: TOBACCO LEAF 15 [hp_X]/1 g; ECHINACEA, UNSPECIFIED 6 [hp_X]/1 g; TARAXACUM OFFICINALE 6 [hp_X]/1 g; VALERIAN 6 [hp_X]/1 g; CHIONANTHUS VIRGINICUS BARK 15 [hp_X]/1 g; CINCHONA OFFICINALIS BARK 15 [hp_X]/1 g; DAPHNE ODORA BARK 15 [hp_X]/1 g; STRYCHNOS IGNATII SEED 15 [hp_X]/1 g; IRIS VERSICOLOR ROOT 15 [hp_X]/1 g; LYCOPODIUM CLAVATUM SPORE 15 [hp_X]/1 g; NICOTINE 15 [hp_X]/1 g; STRYCHNOS NUX-VOMICA SEED 15 [hp_X]/1 g; TOXICODENDRON PUBESCENS LEAF 15 [hp_X]/1 g; SCUTELLARIA LATERIFLORA WHOLE 15 [hp_X]/1 g; ARSENIC TRIOXIDE 15 [hp_X]/1 g; BENZOIC ACID 15 [hp_X]/1 g; BERBERIS VULGARIS ROOT BARK 15 [hp_X]/1 g; BRYONIA ALBA ROOT 15 [hp_X]/1 g; DIEFFENBACHIA SEGUINE 15 [hp_X]/1 g; LYTTA VESICATORIA 15 [hp_X]/1 g; CEANOTHUS AMERICANUS LEAF 15 [hp_X]/1 g; CHELIDONIUM MAJUS 15 [hp_X]/1 g
INACTIVE INGREDIENTS: SUCROSE

Tobacco 2535P

INDICATIONS & USAGE SECTION

Formulated for associated symptoms such as anxiety, cravings, irritability, labored breathing, cough, headaches and stress.

DOSAGE & ADMINISTRATION SECTION

Directions: Adults, take 6 pellets by mouth as needed or as directed by a health professional. Sensitive persons begin with 1 pellet and gradually increase to full dose.

OTC - ACTIVE INGREDIENT SECTION

Equal parts of Echinacea 6x, Taraxacum 6x, Valeriana 6x, Arsenicum alb. 15x, Benzoicum acidum 15x, Berber. vulg. 15x, Bryonia 15x, Caladium seguinum 15x, Cantharis 15x, Ceanothus 15x, Chelidonium majus 15x, Chionanthus virginica 15x, Cinchona 15x, Daphne indica 15x, Ignatia 15x, Iris versicolor 15x, Lycopodium 15x, Nicotinum 15x, Nux vom. 15x, Rhus toxicodendron 15x, Scutellaria lateriflora 15x, Tabacum 15x.

OTC - PURPOSE SECTION

Formulated for associated symptoms such as anxiety, cravings, irritability, labored breathing, cough, headaches and stress.

INACTIVE INGREDIENT SECTION

Inactive Ingredients: Gluten-free, non-GMO, organic beet-derived sucrose (lactose-free) pellets.

QUESTIONS SECTION

newtonlabs.net – Questions? 800.448.7256

Newton Laboratories, Inc. FDA Est # 1051203 - Conyers, GA 30013

WARNINGS SECTION

WARNINGS: Keep out of reach of children. Do not use if tamper-evident seal is broken or missing. If symptoms worsen or persist for more than a few days, consult a doctor. If pregnant or breast-feeding, ask a doctor before use.

OTC - PREGNANCY OR BREAST FEEDING SECTION

If pregnant or breast-feeding, ask a doctor before use.

OTC - KEEP OUT OF REACH OF CHILDREN SECTION

Keep out of reach of children.